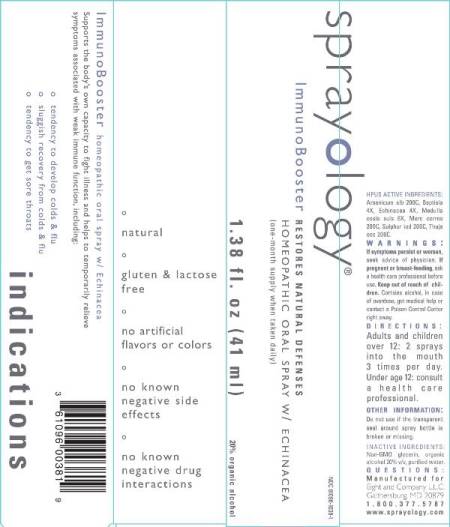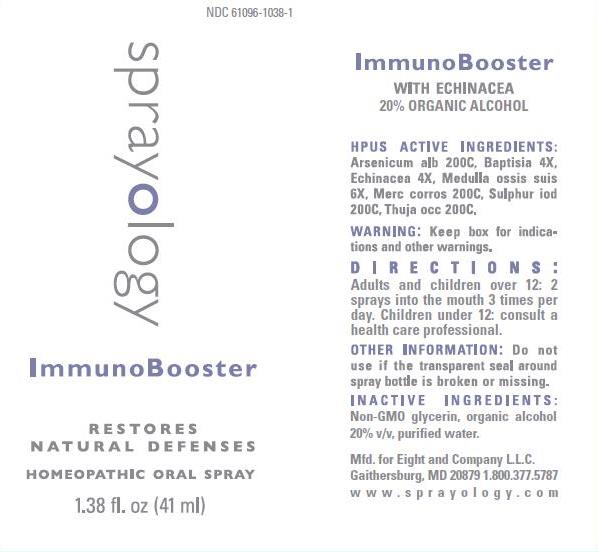 DRUG LABEL: ImmunoBooster
NDC: 61096-1038 | Form: LIQUID
Manufacturer: Eight and Company L.L.C
Category: homeopathic | Type: HUMAN OTC DRUG LABEL
Date: 20251218

ACTIVE INGREDIENTS: ARSENIC TRIOXIDE 200 [hp_C]/41 mL; BAPTISIA TINCTORIA ROOT 4 [hp_X]/41 mL; ECHINACEA, UNSPECIFIED 4 [hp_X]/41 mL; SUS SCROFA BONE MARROW 6 [hp_X]/41 mL; MERCURIC CHLORIDE 200 [hp_C]/41 mL; SULFUR IODIDE 200 [hp_C]/41 mL; THUJA OCCIDENTALIS LEAFY TWIG 200 [hp_C]/41 mL
INACTIVE INGREDIENTS: GLYCERIN; ALCOHOL; WATER

ImmunoBooster

ACTIVE INGREDIENTS:

Arsenicum alb 200C, Baptisia 4X, Echinacea 4X, Medulla ossis suis 6X, Merc corros 200C, Sulphur iod 200C, thuja occ 200C.

PURPOSE:

Supports the body's own capacity to fight illness and helps to temporarily relieve symptoms associated with weak immune function, including:

- tendency to develop colds & Flu
- sluggish recovery from colds & Flu
- tendency to get sore throats

WARNINGS:

If symptoms persist or worsen, seek advice of physician. If pregnant or breast-feeding, ask a health care professional before use. Keep out of reach of children. Contains alcohol, in case of overdose, get medical help or contact a Poison Control Center right away.

Keep out of reach of children. Contains alcohol, in case of overdose, get medical help or contact a Poison Control Center right away.

DIRECTIONS:

Adults and children over 12: 2 sprays into the mouth 3 times per day.

Under age 12: consult a health care professional.

OTHER INFORMATION:

Do not use if the transparent seal around spray bottle is broken or missing.

INDICATIONS:

Supports the body's own capacity to fight illness and helps to temporarily relieve symptoms associated with weak immune function, including:

° tendency to develop colds & flu

° sluggish recovery from colds & flu

° tendency to get sore throats

° natural

° gluten & lactose free

° no artificial flavors or colors

° no known negative side effects

° no known negative drug interactions

INACTIVE INGREDIENTS:

Non-GMO glycerin v/v, organic alcohol 20% v/v and purified water.

QUESTIONS:

Mfd. for Eight and Company L.L.C.

Gaithersburg, MD 20879 1.800.377.5787

www.sprayology.com

PACKAGE LABEL DISPLAY:

NDC 61096-1038-1

sprayology

ImmunoBooster

RESTORES NATURAL DEFENSES

HOMEOPATHIC ORAL SPRAY

1.38 fl.oz (41 ml)